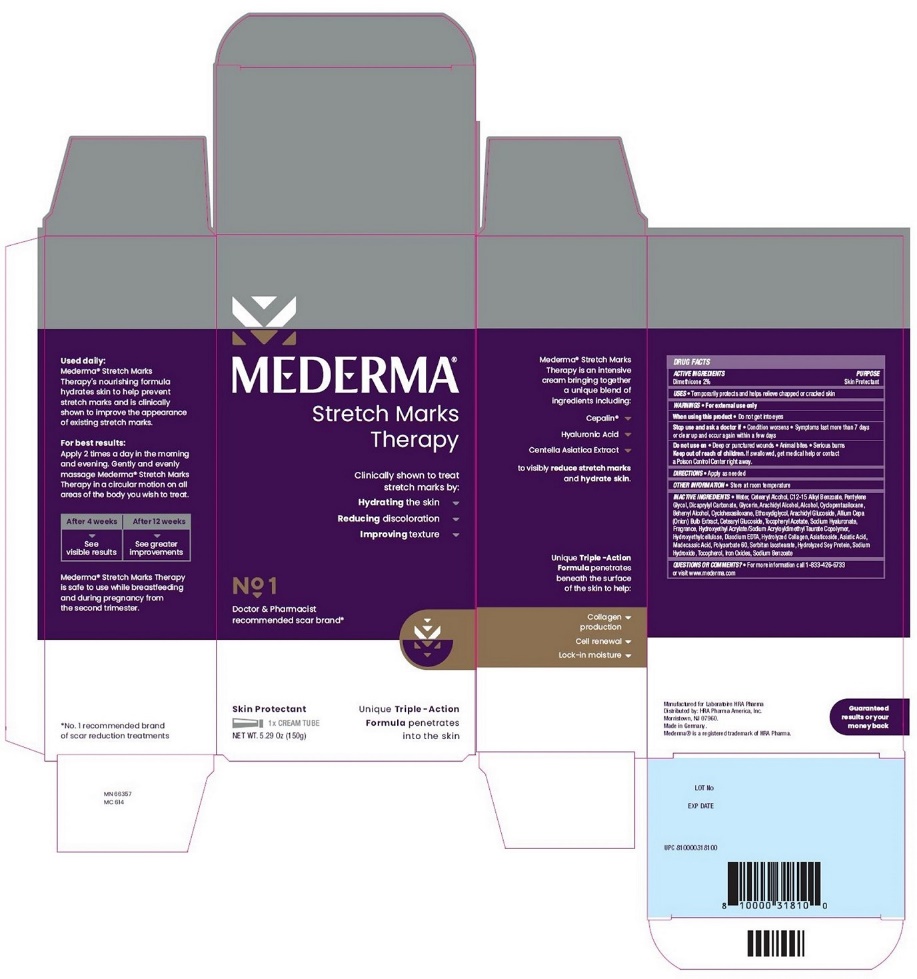 DRUG LABEL: Mederma Stretch Marks Therapy
NDC: 73302-204 | Form: CREAM
Manufacturer: HRA PHARMA AMERICA, INC.
Category: otc | Type: HUMAN OTC DRUG LABEL
Date: 20250127

ACTIVE INGREDIENTS: dimethicone 2 g/100 g
INACTIVE INGREDIENTS: water; Cetostearyl Alcohol; Alkyl (C12-15) Benzoate; Pentylene Glycol; Dicaprylyl Carbonate; Glycerin; Arachidyl Alcohol; Alcohol; Cyclomethicone 5; Docosanol; Cyclomethicone 6; Diethylene Glycol Monoethyl Ether; Arachidyl Glucoside; Onion; Cetearyl Glucoside; .Alpha.-Tocopherol Acetate; Hyaluronate Sodium; Hydroxyethyl Acrylate/Sodium Acryloyldimethyl Taurate Copolymer (100000 Mpa.S At 1.5%); Hydroxyethyl Cellulose (2000 Mpa.S At 1%); Edetate Disodium Anhydrous; Bovine Type I Collagen; Asiaticoside; Asiatic Acid; Madecassic Acid; Polysorbate 60; Sorbitan Isostearate; Soy Protein; Sodium Hydroxide; Tocopherol; Ferric Oxide Red; Sodium Benzoate

Mederma Stretch Marks Therapy DRUG FACTS

Active Ingredients

Dimethicone 2%

Purpose

Skin Protectant

Uses

- Temporarily protects and helps relieve chapped or cracked skin

Warnings

- For external use only

When using this product

- Do not get into eyes

Stop use and ask a doctor if

- Condition worsens
- Symptoms last more than 7 days or clear up and occur again within a few days

Do not use on

- Deep or punctured wounds
- Animal bites
- Serious burns

Keep out of reach of children

If swallowed, get medical help or contact a Poison Control Center right away.

Directions

- Apply as needed

Other Information

- Store at room temperature

Inactive Ingredients

- Water, Cetearyl Alcohol, C12-15 Alkyl Benzoate, Pentylene Glycol, Dicaprylyl Carbonate, Glycerin, Arachidyl Alcohol, Alcohol, Cyclopentasiloxane, Behenyl Alcohol, Cyclohexasiloxane, Ethoxydiglycol, Arachidyl Glucoside, Allium Cepa (Onion) Bulb Extract, Cetearyl Glucoside, Tocopheryl Acetate, Sodium Hyaluronate, Fragrance, Hydroxyethyl Acrylate/Sodium Acryloyldimethyl Taurate Copolymer, Hydroxyethylcellulose, Disodium EDTA, Hydrolyzed Collagen, Asiaticoside, Asiatic Acid, Madecassic Acid, Polysorbate 60, Sorbitan Isostearate, Hydrolyzed Soy Protein, Sodium Hydroxide, Tocopherol, Iron Oxides, Sodium Benzoate

Questions or Comments?

- For more information call 1-833-426-6733 or visit www.mederma.com

PRINCIPAL DISPLAY PANEL

MEDERMA®
Stretch Marks
Therapy
Clinically shown to treat stretch marks by:

● Hydrating the skin

● Reducing discoloration

● Improving texture

No 1
Doctor & Pharmacist recommended scar brand
Skin Protectant
1x CREAM TUBE
NET WT. 5.29 Oz (150g)
Unique Triple-Action Formula penetrates into the skin